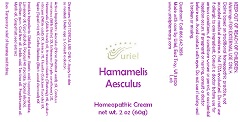 DRUG LABEL: Hamamelis Aesculus
NDC: 48951-5032 | Form: CREAM
Manufacturer: Uriel Pharmacy Inc.
Category: homeopathic | Type: HUMAN OTC DRUG LABEL
Date: 20190219

ACTIVE INGREDIENTS: HORSE CHESTNUT 2 [hp_X]/1 g; MILK THISTLE 2 [hp_X]/1 g; ECHINACEA, UNSPECIFIED 2 [hp_X]/1 g; HAMAMELIS VIRGINIANA ROOT BARK/STEM BARK 2 [hp_X]/1 g; KRAMERIA LAPPACEA WHOLE 2 [hp_X]/1 g; NITRIC ACID 7 [hp_X]/1 g; ARNICA MONTANA 7 [hp_X]/1 g; CALCIUM FLUORIDE 9 [hp_X]/1 g; SEPIA OFFICINALIS JUICE 9 [hp_X]/1 g; ACTIVATED CHARCOAL 11 [hp_X]/1 g
INACTIVE INGREDIENTS: WATER; STEARIC ACID; ISOPROPYL MYRISTATE; LAVENDER OIL; CETYL ALCOHOL; POLYOXYL 40 STEARATE; STEARYL ALCOHOL; XANTHAN GUM; FRANKINCENSE OIL; MYRRH OIL; CITRUS PARADISI SEED; TEA TREE OIL; SORBIC ACID

Hamamelis Aesculus

INDICATIONS AND USAGE

Directions: FOR TOPICAL USE ONLY.

DOSAGE AND ADMINISTRATION

Apply to skin as needed. Under age 2: Consult a doctor.

ACTIVE INGREDIENT

Active Ingredients: Aesculus (Horse chestnut seed) 2X, Carduus marianus (Milk thistle) 2X, Echinacea (Purple coneflower) 2X, Hamamelis (Witch hazel) 2X, Krameria triadra (Rhatany) 2X, Acidum nitricum (Nitric acid) 7X, Arnica 7X, Fluorite (Calcium fluoride) 9X, Sepia (Squid ink) 9X, Carbo Betulae (Birch wood charcoal) 11X

INACTIVE INGREDIENT

Inactive Ingredients: Distilled water, Stearic acid, Isopropyl myristate, Lavender oil, Cetyl alcohol, Polyoxyl 40 stearate, Stearyl alcohol, Xanthan gum, Cod liver oil, Sorbic acid, Tea tree oil, Frankincense oil, Myrrh oil, Grapefruit seed extract

PURPOSE

Uses: Temporary relief of burning and itching.

KEEP OUT OF REACH OF CHILDREN.

Warnings: FOR EXTERNAL USE ONLY.
Claims based on traditional homeopathic practice, not accepted medical evidence. Not FDA evaluated. Do not use if allergic to any ingredient. Consult a doctor before use for serious conditions, if conditions worsen or persist, or accidental ingestion occurs. If pregnant or nursing, consult a doctor before use. Avoid contact with eyes. Do not use if safety seal is broken or missing.

QUESTIONS

Questions? Call 866.642.2858 Made with care by Uriel, East Troy, WI 53120 www.urielpharmacy.com